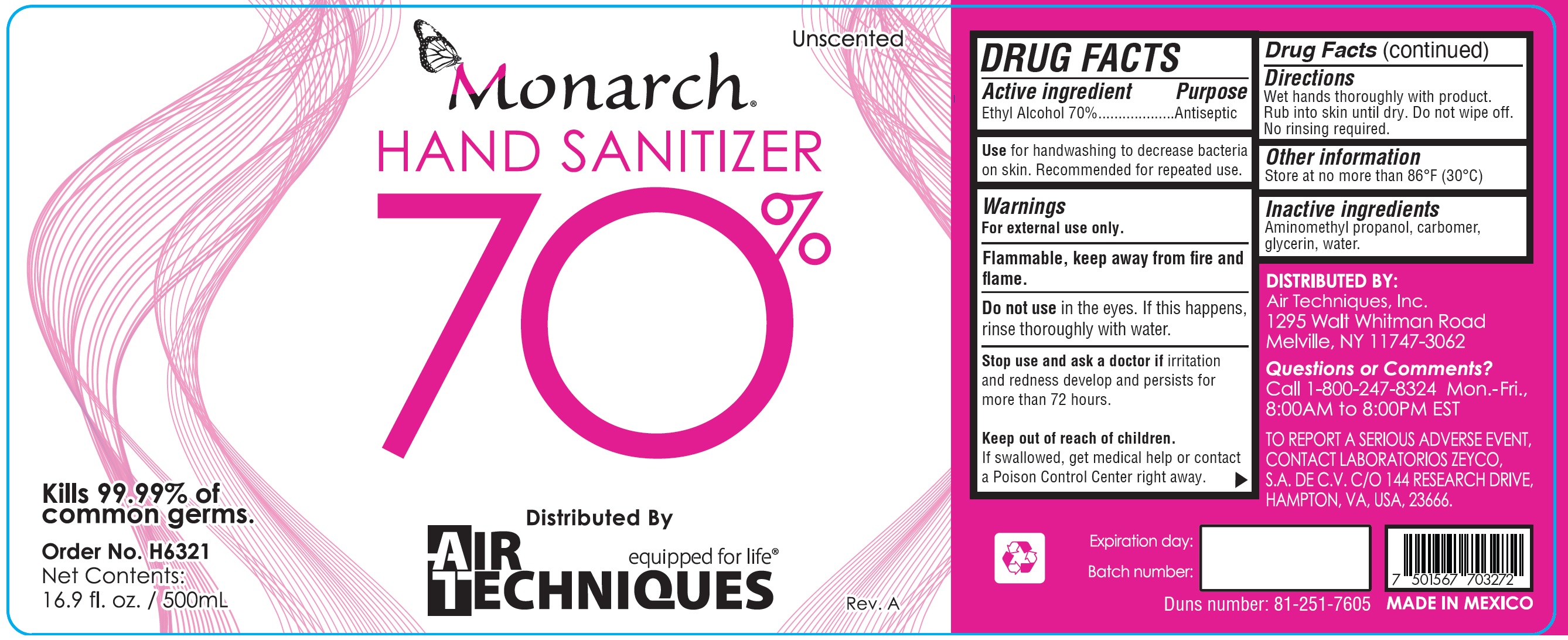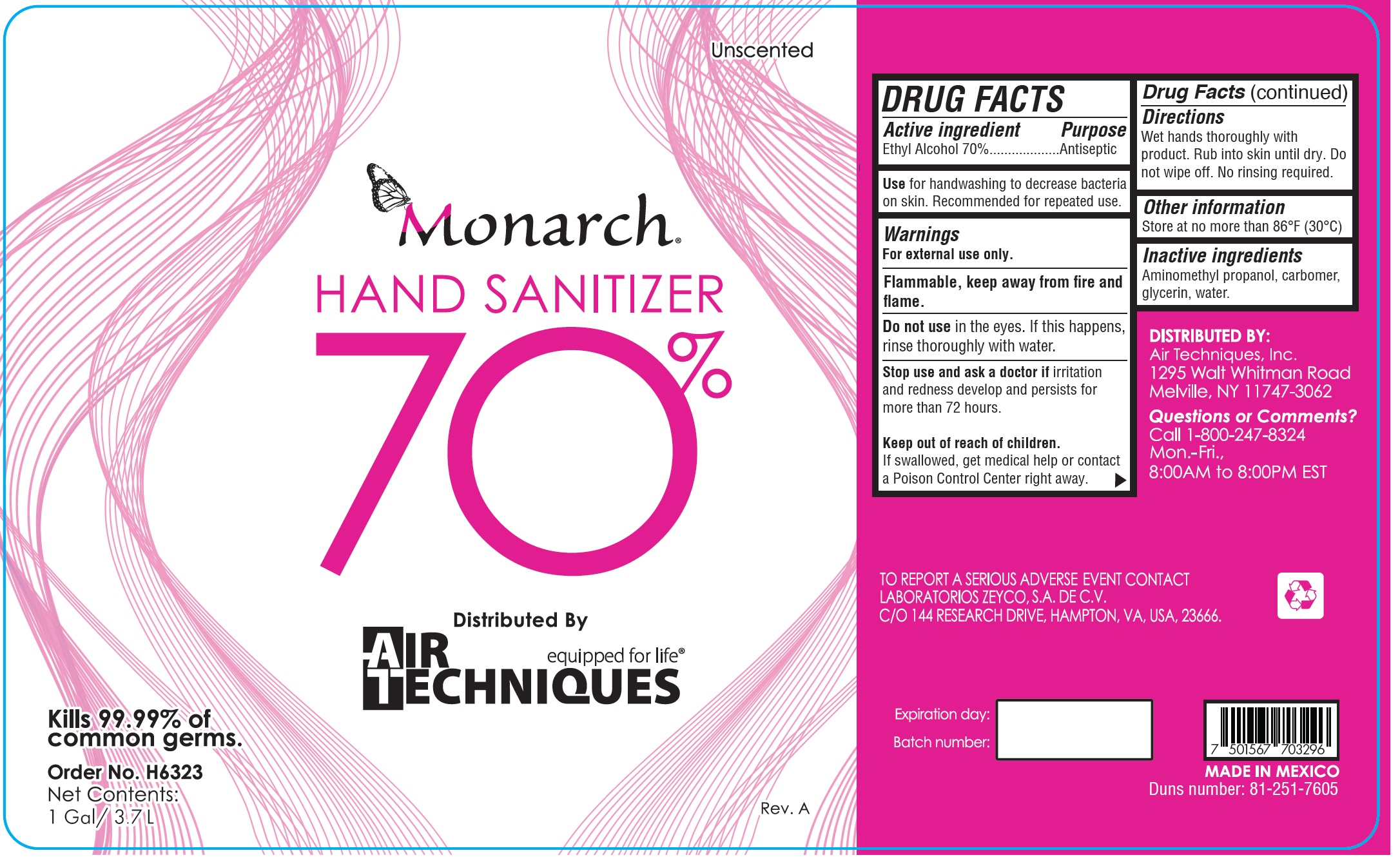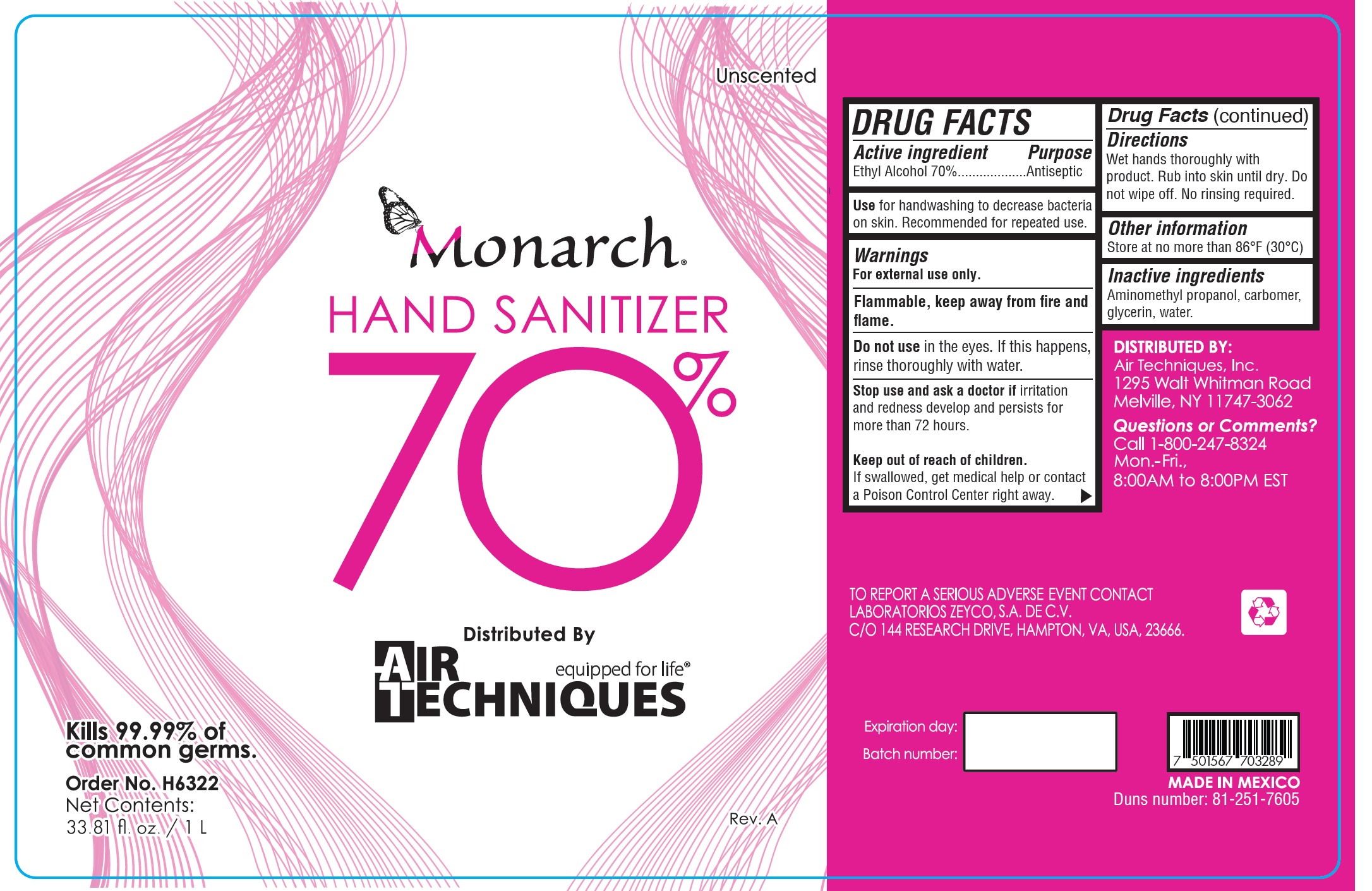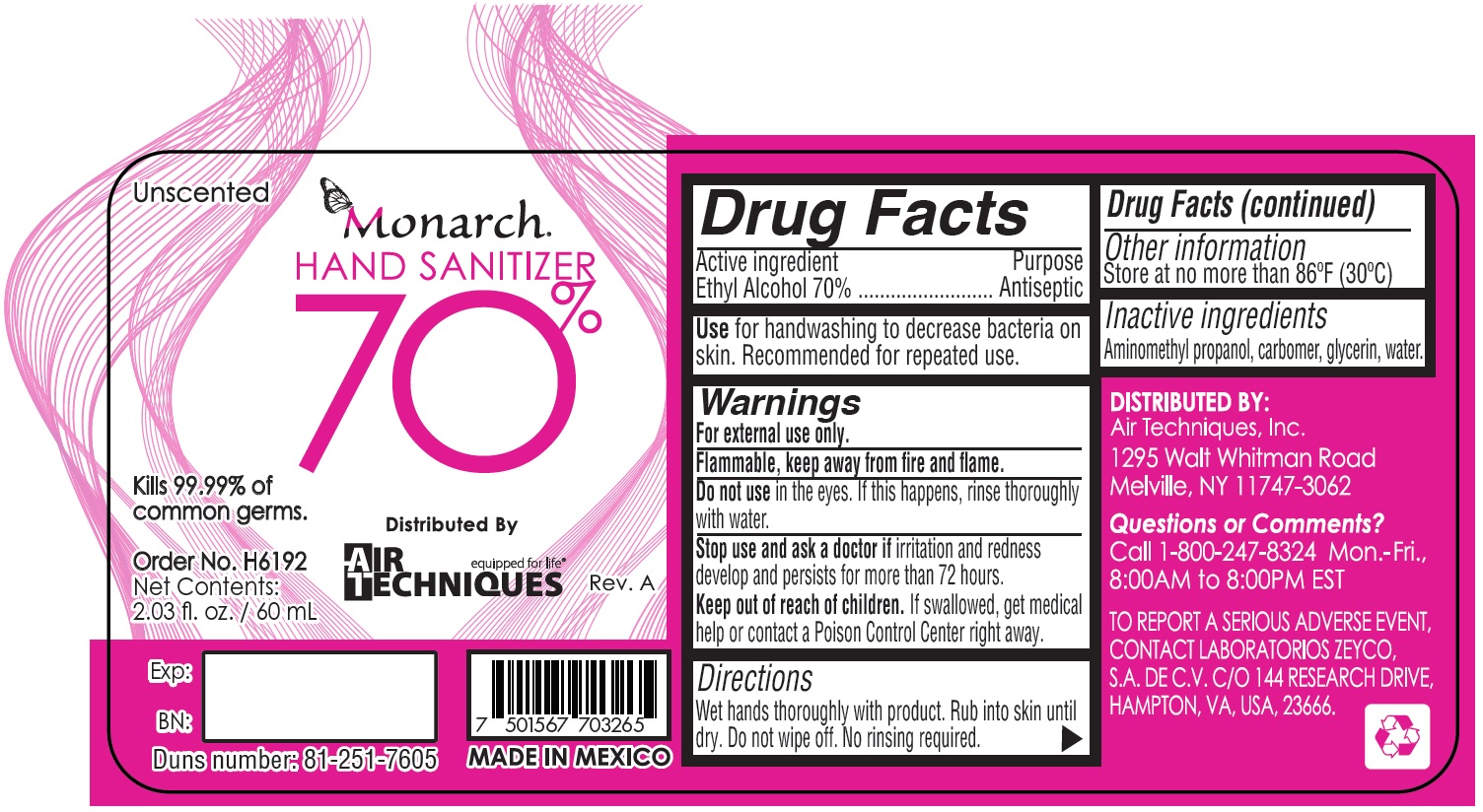 DRUG LABEL: Monarch Hand Sanitizer
NDC: 63710-005 | Form: GEL
Manufacturer: Laboratorios Zeyco, S.A. de C.V.
Category: otc | Type: HUMAN OTC DRUG LABEL
Date: 20231026

ACTIVE INGREDIENTS: ALCOHOL 0.7 L/1 L
INACTIVE INGREDIENTS: AMINOMETHYLPROPANOL; CARBOMER HOMOPOLYMER, UNSPECIFIED TYPE; GLYCERIN; WATER

Monarch Hand Sanitizer 70%

Active ingredient

Ethyl Alcohol 70%

Purpose

Antiseptic

Use

for handwashing to decrease bacteria on skin. Recommended for repeated use.

Warnings

For external use only.

Flammable, keep away from fire and flame.

Do not use

in the eyes. If this happens, rinse thoroughly with water.

Stop use and ask a doctor if

irritation and redness develop and persists for more than 72 hours.

Keep out of reach of children.

If swallowed, get medical help or contact a Poison Control Center right away.

Directions

Wet hands thoroughly with product. Rub into skin until dry. Do not wipe off. No rinsing required.

Other information

Store at no more than 86°F (30°C)

Inactive ingredients

Aminomethyl propanol, carbomer, glycerin, water.